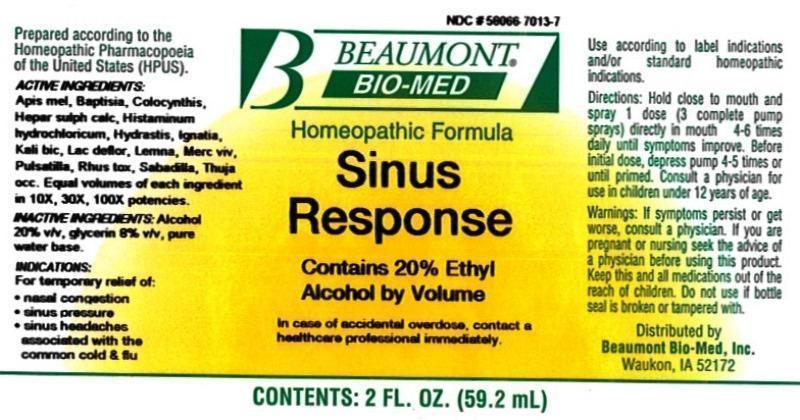 DRUG LABEL: Sinus Response
NDC: 58066-7013 | Form: LIQUID
Manufacturer: Beaumont Bio Med
Category: homeopathic | Type: HUMAN OTC DRUG LABEL
Date: 20160912

ACTIVE INGREDIENTS: APIS MELLIFERA 10 [hp_X]/59.2 mL; BAPTISIA TINCTORIA ROOT 10 [hp_X]/59.2 mL; CITRULLUS COLOCYNTHIS FRUIT PULP 10 [hp_X]/59.2 mL; CALCIUM SULFIDE 10 [hp_X]/59.2 mL; HISTAMINE DIHYDROCHLORIDE 10 [hp_X]/59.2 mL; GOLDENSEAL 10 [hp_X]/59.2 mL; STRYCHNOS IGNATII SEED 10 [hp_X]/59.2 mL; POTASSIUM DICHROMATE 10 [hp_X]/59.2 mL; SKIM MILK 10 [hp_X]/59.2 mL; LEMNA MINOR 10 [hp_X]/59.2 mL; MERCURY 10 [hp_X]/59.2 mL; PULSATILLA VULGARIS 10 [hp_X]/59.2 mL; TOXICODENDRON PUBESCENS LEAF 10 [hp_X]/59.2 mL; SCHOENOCAULON OFFICINALE SEED 10 [hp_X]/59.2 mL; THUJA OCCIDENTALIS LEAFY TWIG 10 [hp_X]/59.2 mL
INACTIVE INGREDIENTS: WATER; ALCOHOL; GLYCERIN

Sinus Response

ACTIVE INGREDIENT

HPUS active ingredients: Apis mellifica, Baptisia tinctoria, Colocynthis, Hepar sulphuris calcareum, Histaminum hydrochloricum, Hydrastis canadensis, Ignatia amara, Kali bichromicum, Lac defloratum, Lemna minor, Mercurius vivus, Pulsatilla, Rhus toxicodendron, Sabadilla, Thuja occidentalis. Equal volumes of each ingredient in 10X, 30X, 100X potencies.

INACTIVE INGREDIENT

Inactive Ingredients: Alcohol (20% v/v), Glycerin (8% v/v), in a pure water base.

INDICATIONS AND USAGE

Indications: For temporary relief of: nasal congestion, sinus pressure, sinus headaches associated with the common cold and flu.

Directions:

- Hold close to mouth and spray 1 dose (3 complete pump sprays) directly in mouth 4-6 times daily until symptoms improve.
- Before initial dose, depress pump 4-5 times or until primed.
- Consult a physician for use in children under 12 years of age.

Use according to label indications and/or standard homeopathic indications

WARNINGS

Warnings: If symptoms persist or get worse, consult a physician. If you are pregnant or nursing seek the advice of a physician before using this product.

KEEP OUT OF REACH OF CHILDREN

- Keep this and all medications out of the reach of children.

Other Information: Do not use if bottle seal is broken or tampered with.

PURPOSE

For temporary relief of:

- nasal congestion
- sinus pressure
- sinus headaches associated with the common cold and flu